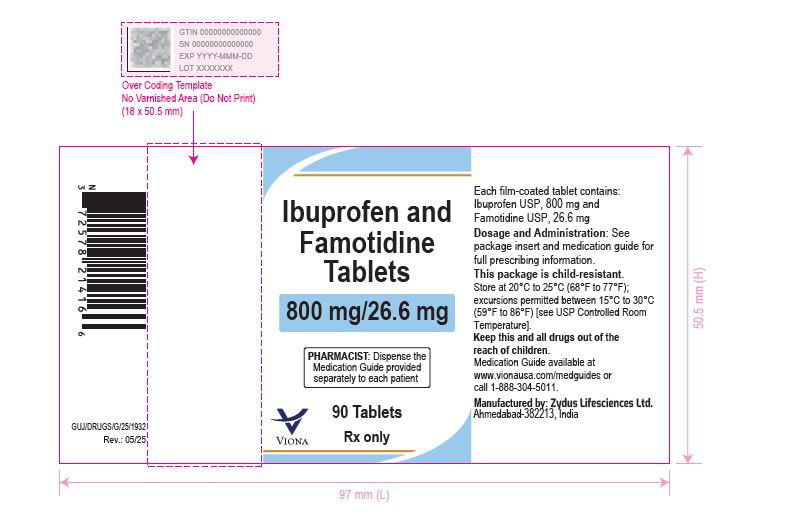 DRUG LABEL: Ibuprofen and Famotidine
NDC: 70771-1924 | Form: TABLET
Manufacturer: Zydus Lifesciences Limited
Category: prescription | Type: HUMAN PRESCRIPTION DRUG LABEL
Date: 20250528

ACTIVE INGREDIENTS: IBUPROFEN 800 mg/1 1; FAMOTIDINE 26.6 mg/1 1
INACTIVE INGREDIENTS: CROSCARMELLOSE SODIUM; FERROSOFERRIC OXIDE; GLYCERYL MONO- AND DICAPRYLOCAPRATE; HYPROMELLOSE 2910 (15 MPA.S); MAGNESIUM STEARATE; MICROCRYSTALLINE CELLULOSE; POLYVINYL ALCOHOL, UNSPECIFIED; PROPYLENE GLYCOL; SHELLAC; SILICON DIOXIDE; SODIUM LAURYL SULFATE; TALC; TITANIUM DIOXIDE

Ibuprofen and Famotidine Tablets

PACKAGE LABEL.PRINCIPAL DISPLAY PANEL

Ibuprofen and famotidine tablets, 800 mg/26.6 mg

90 Tablets

NDC 70771-1924-9

Rx only